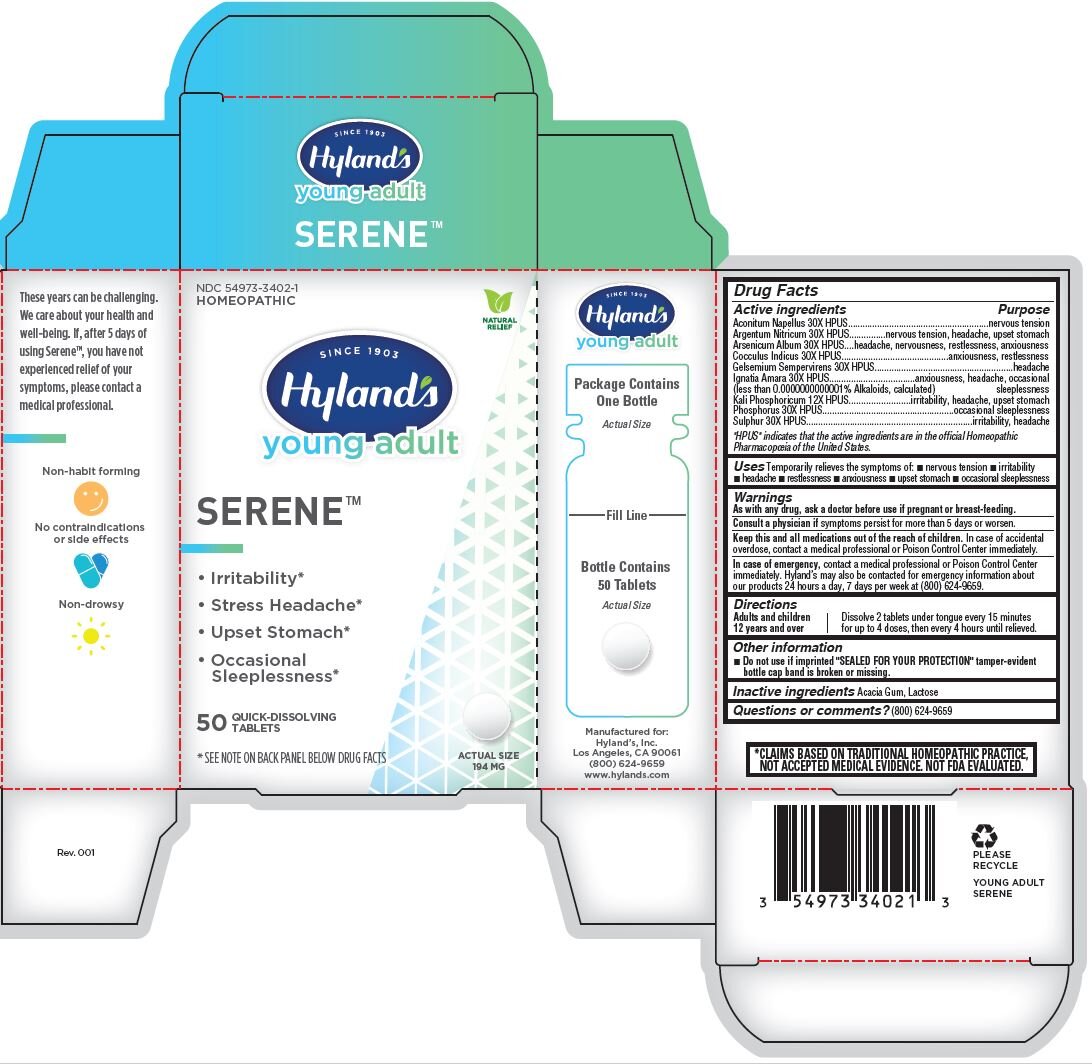 DRUG LABEL: Young Adult Serene
NDC: 54973-3402 | Form: TABLET
Manufacturer: Hyland's Inc.
Category: homeopathic | Type: HUMAN OTC DRUG LABEL
Date: 20221214

ACTIVE INGREDIENTS: GELSEMIUM SEMPERVIRENS ROOT 30 [hp_X]/1 1; POTASSIUM PHOSPHATE, DIBASIC 12 [hp_X]/1 1; ARSENIC TRIOXIDE 30 [hp_X]/1 1; SILVER NITRATE 30 [hp_X]/1 1; STRYCHNOS IGNATII SEED 30 [hp_X]/1 1; ANAMIRTA COCCULUS SEED 30 [hp_X]/1 1; ACONITUM NAPELLUS 30 [hp_X]/1 1; PHOSPHORUS 30 [hp_X]/1 1; SULFUR 30 [hp_X]/1 1
INACTIVE INGREDIENTS: LACTOSE MONOHYDRATE; ACACIA

Hyland's Young Adult SERENE™

Drug Facts

Active ingredients

Aconitum Napellus 30X HPUS

Argentum Nitricum 30X HPUS

Arsenicum Album 30X HPUS

Cocculus Indicus 30X HPUS

Gelsemium Sempervirens 30X HPUS

Ignatia Amara 30X HPUS

(less than 0.0000000000001% Alkaloids, calculated)

Kali Phosphoricum 12X HPUS

Phosphorus 30X HPUS

Sulphur 30X HPUS

"HPUS" indicates that the active ingredients are in the official Homeopathic

Pharmacopoeia of the United States.

Uses

Temporarily relieves the symptoms of: nervous tension, irritability, headache, restlessness, anxiousness, upset stomach, occasional sleeplessness

PURPOSE

• Irritability*

• Stress Headache*

• Upset Stomach*

• Occasional Sleeplessness*

Warnings

As with any drug, ask a doctor before use if pregnant or breast-feeding.

Consult a physician if symptoms persist for more than 5 days or worsen.

KEEP OUT OF REACH OF CHILDREN

Keep this and all medications out of the reach of children. In case of accidental

overdose, contact a medical professional or Poison Control Center immediately.

In case of emergency, contact a medical professional or Poison Control Center immediately. Hyland’s may also be contacted for emergency information about our products 24 hours a day, 7 days per week at (800) 624-9659.

Directions

Adults and children

12 years and over

Dissolve 2 tablets under tongue every 15 minutes

for up to 4 doses, then every 4 hours until relieved.

Other information

- Do not use if imprinted "SEALED FOR YOUR PROTECTION" tamper-evident bottle cap band is broken or missing.

Inactive ingredients

Acacia Gum, Lactose

Questions or comments?

(800) 624-9659

*CLAIMS BASED ON TRADITIONAL HOMEOPATHIC PRACTICE,

NOT ACCEPTED MEDICAL EVIDENCE. NOT FDA EVALUATED.

Principal DIsplay Panel - 50 Tablet Bottle Carton

NDC 54973-3402-1

HOMEOPATHIC

NATURAL

RELIEF

SINCE 1903

Hyland's

young adult

SERENE™

- Irritability*
- Stress Headache*
- Upset Stomach*
- Occasional Sleeplessness*

50 QUICK-DISSOLVING

TABLETS

*SEE NOTE ON BACK PANEL BELOW DRUG FACTS

ACTUAL SIZE

194 MG